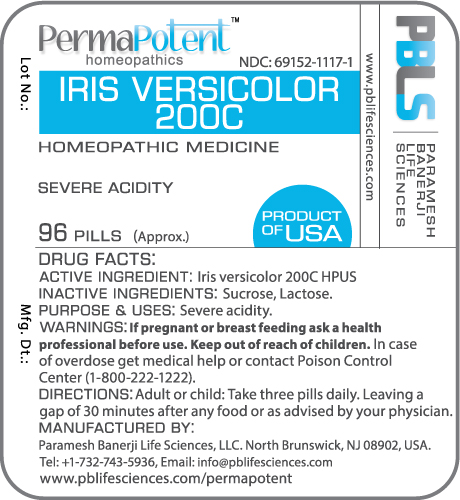 DRUG LABEL: Iris versicolor 200C
NDC: 69152-1117 | Form: PELLET
Manufacturer: Paramesh Banerji Life Sciences LLC
Category: homeopathic | Type: HUMAN OTC DRUG LABEL
Date: 20160923

ACTIVE INGREDIENTS: IRIS VERSICOLOR ROOT 200 [hp_C]/1 1
INACTIVE INGREDIENTS: SUCROSE; LACTOSE

DRUG FACTS: Active Ingredient

Iris versicolor 200C HPUS

Inactive Ingredients

Sucrose, Lactose

Purpose

Severe acidity

Uses

Severe acidity

Warnings

If pregnant or breast feeding ask a health professional before use.

Keep out of reach of children. In case of overdose, get medical help or contact a Poison Control Center (1-800-222-1222) right away.

Direction

Adult or child: Take three pills daily. Leaving a gap of 30 minutes after any food or as advised by your physician.

Manufactured by

Paramesh Banerji Life Sciences, LLC.

North Brunswick, NJ 08902, USA.

Tel: +1-732-743-5936,

Email: info@pblifesciences.com

www.pblifesciences.com/permapotent

Principal Display Panel

NDC: 69152-1117-1

Iris versicolor 200C

Homeopathic Medicine

Severe acidity

96 Pills (Approx.)

Product of USA